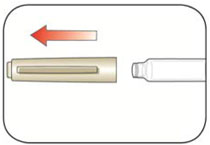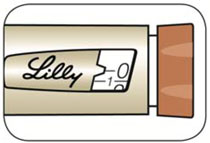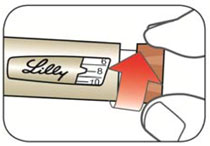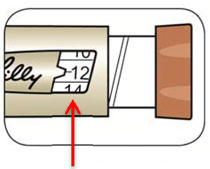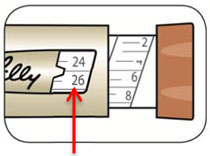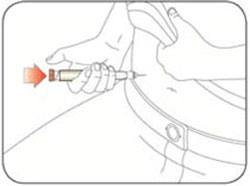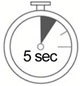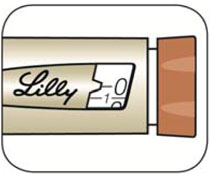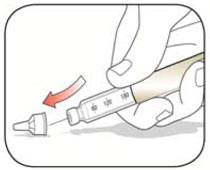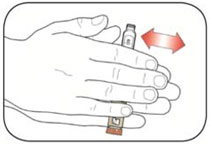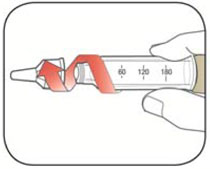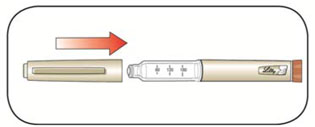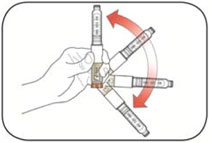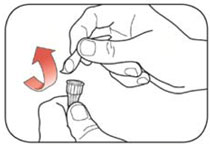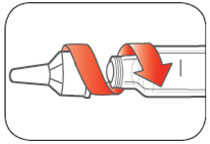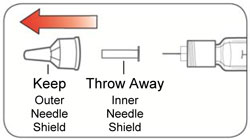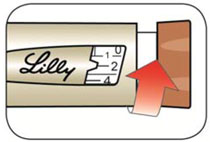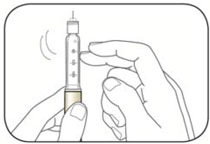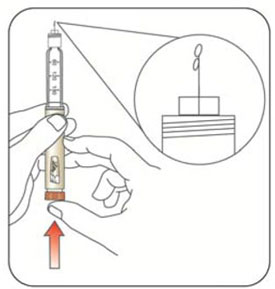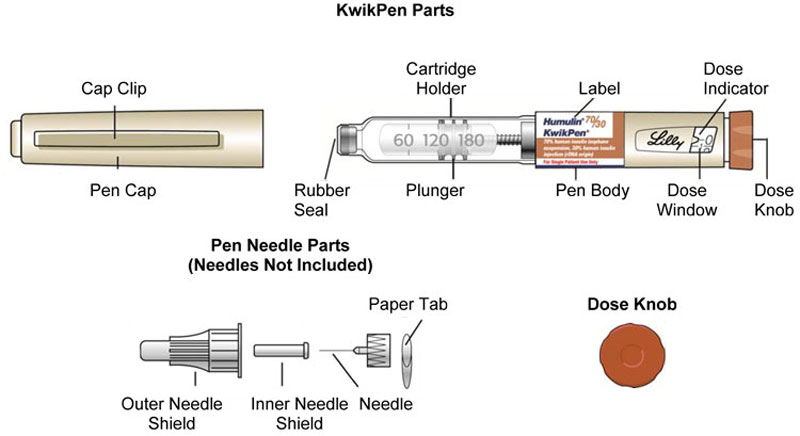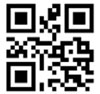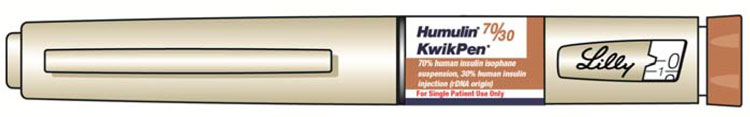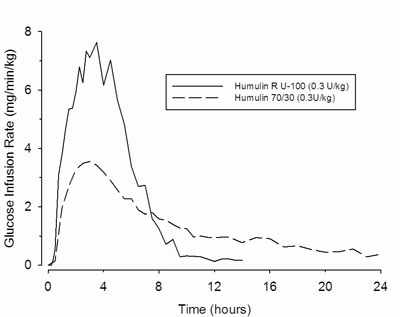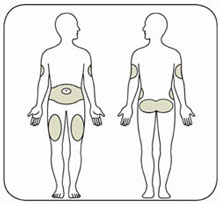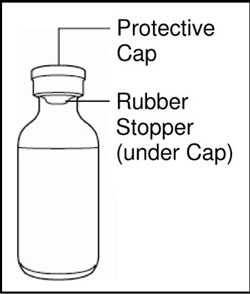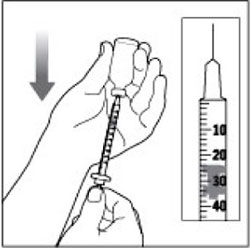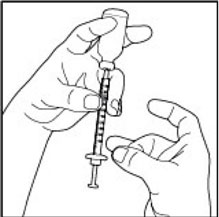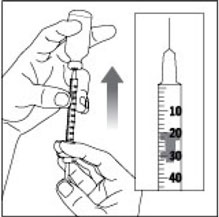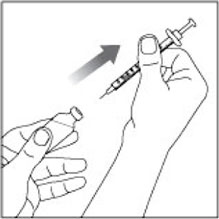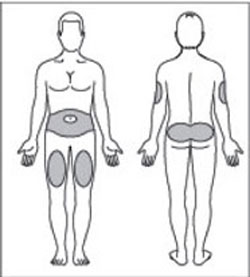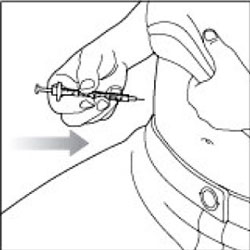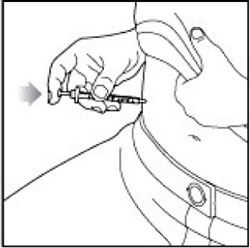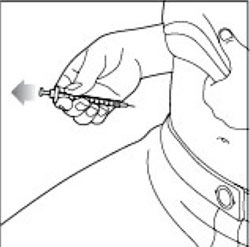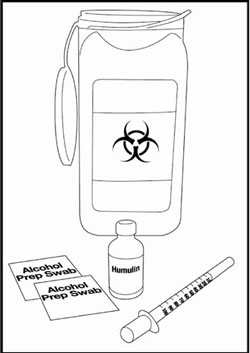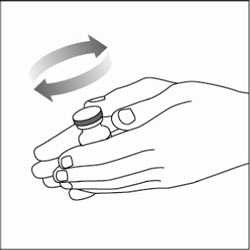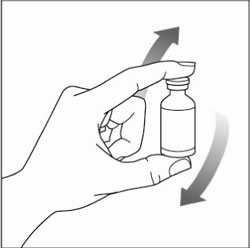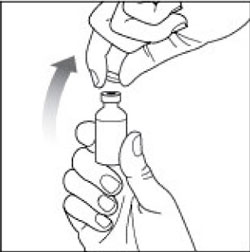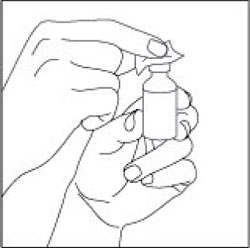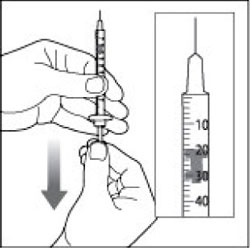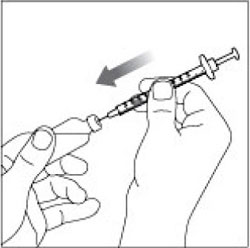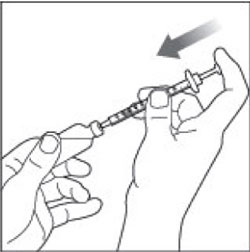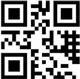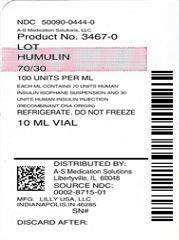 DRUG LABEL: Humulin 
NDC: 50090-0444 | Form: INJECTION, SUSPENSION
Manufacturer: A-S Medication Solutions
Category: otc | Type: HUMAN OTC DRUG LABEL
Date: 20171012

ACTIVE INGREDIENTS: INSULIN HUMAN 100 [iU]/1 mL
INACTIVE INGREDIENTS: Glycerin 16 mg/1 mL; Metacresol 1.6 mg/1 mL; Zinc 0.025 mg/1 mL; Phenol 0.65 mg/1 mL; Protamine sulfate 0.241 mg/1 mL; SODIUM PHOSPHATE, DIBASIC, UNSPECIFIED FORM 3.78 mg/1 mL; Water; Hydrochloric acid; Sodium hydroxide

HIGHLIGHTS OF PRESCRIBING INFORMATION

These highlights do not include all the information needed to use HUMULIN 70/30 safely and effectively. See full prescribing information for HUMULIN 70/30.
HUMULIN® 70/30 (70% human insulin isophane suspension and 30% human insulin injection [rDNA origin]) injectable suspension, for subcutaneous use
Initial U.S. Approval: 1989

RECENT MAJOR CHANGES

None.

1 INDICATIONS AND USAGE

HUMULIN 70/30 is an insulin indicated to improve glycemic control in adult patients with diabetes mellitus. (1)

2 DOSAGE AND ADMINISTRATION

- Only administer subcutaneously (in abdominal wall, thigh, upper arm, or buttocks). (2.2)
- Individualize and adjust dosage based on metabolic needs, blood glucose monitoring results and glycemic control goal. (2.3)
- See Full Prescribing Information for dosage adjustments due to drug interactions and patients with renal and hepatic impairment. (2.3)
- Administer approximately 30-45 minutes before a meal. (2.4)

3 DOSAGE FORMS AND STRENGTHS

Injectable suspension 100 units per mL (U-100) available as 10 mL vials, 3 mL vials, and 3 mL HUMULIN® 70/30 KwikPen® (prefilled). (3)

4 CONTRAINDICATIONS

- During episodes of hypoglycemia. (4)
- In patients with hypersensitivity to HUMULIN 70/30 or any of its excipients. (4)

5 WARNINGS AND PRECAUTIONS

- Never share a HUMULIN 70/30 KwikPen or syringe between patients, even if the needle is changed. (5.1)
- Changes in Insulin Regimen: Carry out under close medical supervision and increase frequency of blood glucose monitoring. (5.2)
- Hypoglycemia: May be life-threatening. Monitor blood glucose and increase monitoring frequency with changes to insulin dosage, use of glucose lowering medications, meal pattern, physical activity; in patients with renal or hepatic impairment; and in patients with hypoglycemia unawareness. (5.3, 7, 8.6, 8.7)
- Hypersensitivity Reactions: May be life-threatening. Discontinue HUMULIN 70/30, monitor and treat if indicated. (5.4)
- Hypokalemia: May be life-threatening. Monitor potassium levels in patients at risk of hypokalemia and treat if indicated. (5.5)
- Fluid Retention and Heart Failure with Concomitant Use of Thiazolidinediones (TZDs): Observe for signs and symptoms of heart failure; consider dosage reduction or discontinuation if heart failure occurs. (5.6)

6 ADVERSE REACTIONS

Adverse reactions observed with insulin therapy include hypoglycemia, allergic reactions, injection site reactions, lipodystrophy, pruritus, rash, weight gain, and edema. (6)

To report SUSPECTED ADVERSE REACTIONS, contact Eli Lilly and Company at 1-800-LillyRx (1-800-545-5979) or FDA at 1-800-FDA-1088 or www.fda.gov/medwatch.

7 DRUG INTERACTIONS

- Drugs that Affect Glucose Metabolism: Adjustment of insulin dosage may be needed. (7.1, 7.2, 7.3)
- Anti-Adrenergic Drugs (e.g., beta-blockers, clonidine, guanethidine, and reserpine): Signs and symptoms of hypoglycemia may be reduced or absent. (5.3, 7.4)

FULL PRESCRIBING INFORMATION

1 INDICATIONS AND USAGE

HUMULIN 70/30 is a fixed ratio premix recombinant human insulin formulation indicated to improve glycemic control in adult patients with diabetes mellitus.

2 DOSAGE AND ADMINISTRATION

2.1 Important Administration Instructions

Inspect HUMULIN 70/30 visually before use. It should not contain particulate matter and should appear uniformly cloudy after mixing. Do not use HUMULIN 70/30 if particulate matter is seen. Do not mix HUMULIN 70/30 with any other insulins or diluents.

2.2 Route of Administration

HUMULIN 70/30 should only be administered subcutaneously. Administer in the subcutaneous tissue of the abdominal wall, thigh, upper arm, or buttocks. To reduce the risk of lipodystrophy, rotate the injection site within the same region from one injection to the next [see Adverse Reactions (6)].

Do not administer HUMULIN 70/30 intravenously or intramuscularly and do not use HUMULIN 70/30 in an insulin infusion pump.

2.3 Dosage Information

Individualize and adjust the dosage of HUMULIN 70/30 based on the individual's metabolic needs, blood glucose monitoring results and glycemic control goal. Dosage adjustments may be needed with changes in physical activity, changes in meal patterns (i.e., macronutrient content or timing of food intake), changes in renal or hepatic function or during acute illness [see Warnings and Precautions (5.2, 5.3), and Use in Specific Populations (8.6, 8.7)].

The proportion of rapid acting and long acting insulin is fixed in a premixed insulin such as HUMULIN 70/30. Independent adjustment of the basal or prandial dose is not possible when using a premixed insulin.

Physiological factors, disease states and concomitant drugs may impact the onset and duration of action of all insulins. HUMULIN 70/30 dose requirements may change with changes in level of physical activity, meal patterns (i.e., macronutrient content or timing of food intake), during major illness, or with some coadministered drugs [see Warnings and Precautions (5.3), Drug Interactions (7), and Use in Specific Populations (8.6, 8.7)].

2.4 Timing of Subcutaneous Administration

HUMULIN 70/30 should be given subcutaneously approximately 30-45 minutes before a meal.

3 DOSAGE FORMS AND STRENGTHS

HUMULIN 70/30 injectable suspension: 100 units per mL (U-100) is available as:

- 10 mL vials
- 3 mL vials
- 3 mL HUMULIN 70/30 KwikPen (prefilled)

4 CONTRAINDICATIONS

HUMULIN 70/30 is contraindicated:

- During episodes of hypoglycemia [see Warnings and Precautions (5.3)], and
- In patients who have had hypersensitivity reactions to HUMULIN 70/30 or any of its excipients [see Warnings and Precautions (5.4)].

5 WARNINGS AND PRECAUTIONS

5.1 Never Share a HUMULIN 70/30 KwikPen or Syringe Between Patients

HUMULIN 70/30 KwikPens must never be shared between patients, even if the needle is changed. Patients using HUMULIN 70/30 vials must never share needles or syringes with another person. Sharing poses a risk for transmission of blood-borne pathogens.

5.2 Changes in Insulin Regimen

Changes in insulin strength, manufacturer, type, or method of administration may affect glycemic control and predispose to hypoglycemia [see Warnings and Precautions (5.3)] or hyperglycemia. These changes should be made cautiously and under close medical supervision and the frequency of blood glucose monitoring should be increased.

5.3 Hypoglycemia

Hypoglycemia is the most common adverse reaction associated with insulins, including HUMULIN 70/30. Severe hypoglycemia can cause seizures, may be life-threatening or cause death. Hypoglycemia can impair concentration ability and reaction time; this may place an individual and others at risk in situations where these abilities are important (e.g., driving or operating other machinery).

Hypoglycemia can happen suddenly and symptoms may differ in each individual and change over time in the same individual. Symptomatic awareness of hypoglycemia may be less pronounced in patients with longstanding diabetes, in patients with diabetic nerve disease, in patients using medications that block the sympathetic nervous system (e.g., beta-blockers) [see Drug Interactions (7)], or in patients who experience recurrent hypoglycemia.

Risk Factors for Hypoglycemia

The risk of hypoglycemia after an injection is related to the duration of action of the insulin and, in general, is highest when the glucose lowering effect of the insulin is maximal. As with all insulin preparations, the glucose lowering effect time course of HUMULIN 70/30 may vary in different individuals or at different times in the same individual and depends on many conditions, including the area of injection as well as the injection site blood supply and temperature [see Clinical Pharmacology (12.2)]. Other factors which may increase the risk of hypoglycemia include changes in meal pattern (e.g., macronutrient content or timing of meals), changes in level of physical activity, or changes to co-administered medication [see Drug Interactions (7)]. Patients with renal or hepatic impairment may be at higher risk of hypoglycemia [see Use in Specific Populations (8.6, 8.7)].

Risk Mitigation Strategies for Hypoglycemia

Patients and caregivers must be educated to recognize and manage hypoglycemia. Self-monitoring of blood glucose plays an essential role in the prevention and management of hypoglycemia. In patients at higher risk for hypoglycemia and patients who have reduced symptomatic awareness of hypoglycemia, increased frequency of blood glucose monitoring is recommended.

5.4 Hypersensitivity Reactions

Severe, life-threatening, generalized allergy, including anaphylaxis, can occur with insulin products, including HUMULIN 70/30. If hypersensitivity reactions occur, discontinue HUMULIN 70/30; treat per standard of care and monitor until symptoms and signs resolve [see Adverse Reactions (6)]. HUMULIN 70/30 is contraindicated in patients who have had hypersensitivity reactions to HUMULIN 70/30 or any of its excipients [see Contraindications (4)].

5.5 Hypokalemia

All insulin products, including HUMULIN 70/30, cause a shift in potassium from the extracellular to intracellular space, possibly leading to hypokalemia. Untreated hypokalemia may cause respiratory paralysis, ventricular arrhythmia, and death. Monitor potassium levels in patients at risk for hypokalemia if indicated (e.g., patients using potassium-lowering medications, patients taking medications sensitive to serum potassium concentrations).

5.6 Fluid Retention and Heart Failure with Concomitant Use of PPAR-gamma Agonists

Thiazolidinediones (TZDs), which are peroxisome proliferator-activated receptor (PPAR)-gamma agonists, can cause dose-related fluid retention, particularly when used in combination with insulin. Fluid retention may lead to or exacerbate heart failure. Patients treated with insulin, including HUMULIN 70/30, and a PPAR-gamma agonist should be observed for signs and symptoms of heart failure. If heart failure develops, it should be managed according to current standards of care, and discontinuation or dose reduction of the PPAR-gamma agonist must be considered.

6 ADVERSE REACTIONS

The following adverse reactions are discussed elsewhere in the labeling:

- Hypoglycemia [see Warnings and Precautions (5.3)].
- Hypokalemia [see Warnings and Precautions (5.5)].

The following additional adverse reactions have been identified during post-approval use of HUMULIN 70/30. Because these reactions are reported voluntarily from a population of uncertain size, it is not always possible to reliably estimate their frequency or to establish a causal relationship to drug exposure.

Allergic Reactions

Some patients taking HUMULIN 70/30 have experienced erythema, local edema, and pruritus at the site of injection. These conditions were usually self-limiting. Severe cases of generalized allergy (anaphylaxis) have been reported [see Warnings and Precautions (5.4)].

Peripheral Edema

Some patients taking HUMULIN 70/30 have experienced sodium retention and edema, particularly if previously poor metabolic control is improved by intensified insulin therapy.

Lipodystrophy

Administration of insulin subcutaneously, including HUMULIN 70/30, has resulted in lipoatrophy (depression in the skin) or lipohypertrophy (enlargement or thickening of tissue) [see Dosage and Administration (2.2)] in some patients.

Weight gain

Weight gain has occurred with some insulin therapies including HUMULIN 70/30 and has been attributed to the anabolic effects of insulin and the decrease in glycosuria.

Immunogenicity

Development of antibodies that react with human insulin have been observed with all insulin, including HUMULIN 70/30.

7 DRUG INTERACTIONS

7.1 Drugs That May Increase the Risk of Hypoglycemia

The risk of hypoglycemia associated with HUMULIN 70/30 use may be increased when co-administered with antidiabetic agents, salicylates, sulfonamide antibiotics, monoamine oxidase inhibitors, fluoxetine, disopyramide, fibrates, propoxyphene, pentoxifylline, ACE inhibitors, angiotensin II receptor blocking agents, and somatostatin analogs (e.g., octreotide). Dose adjustment and increased frequency of glucose monitoring may be required when HUMULIN 70/30 is co-administered with these drugs.

7.2 Drugs That May Decrease the Blood Glucose Lowering Effect of HUMULIN 70/30

The glucose lowering effect of HUMULIN 70/30 may be decreased when co-administered with corticosteroids, isoniazid, niacin, estrogens, oral contraceptives, phenothiazines, danazol, diuretics, sympathomimetic agents (e.g., epinephrine, albuterol, terbutaline), somatropin, atypical antipsychotics, glucagon, protease inhibitors, and thyroid hormones. Dose adjustment and increased frequency of glucose monitoring may be required when HUMULIN 70/30 is co-administered with these drugs.

7.3 Drugs That May Increase or Decrease the Blood Glucose Lowering Effect of HUMULIN 70/30

The glucose lowering effect of HUMULIN 70/30 may be increased or decreased when co-administered with beta-blockers, clonidine, lithium salts, and alcohol. Pentamidine may cause hypoglycemia, which may sometimes be followed by hyperglycemia. Dose adjustment and increased frequency of glucose monitoring may be required when HUMULIN 70/30 is co-administered with these drugs.

7.4 Drugs That May Blunt Signs and Symptoms of Hypoglycemia

The signs and symptoms of hypoglycemia [see Warnings and Precautions (5.3)] may be blunted when beta-blockers, clonidine, guanethidine, and reserpine are co-administered with HUMULIN 70/30.

8 USE IN SPECIFIC POPULATIONS

8.1 Pregnancy

Pregnancy Category B

Risk Summary

All pregnancies have a background risk of birth defects, loss, or other adverse outcome regardless of drug exposure. This background risk is increased in pregnancies complicated by hyperglycemia and may be decreased with good metabolic control. It is essential for patients with diabetes or history of gestational diabetes to maintain good metabolic control before conception and throughout pregnancy. In patients with diabetes or gestational diabetes, insulin requirements may decrease during the first trimester, generally increase during the second and third trimesters, and rapidly decline after delivery. Careful monitoring of glucose control is essential in these patients. Therefore, female patients should be advised to tell their physicians if they intend to become, or if they become pregnant while taking HUMULIN 70/30.

Human Data

While there are no adequate and well-controlled studies of HUMULIN 70/30 in pregnant women, evidence from published literature suggests that good glycemic control in patients with diabetes during pregnancy provides significant maternal and fetal benefits.

Animal Data

Reproduction and fertility toxicity studies were not performed in animals.

8.3 Nursing Mothers

Endogenous insulin is present in human milk; it is unknown whether HUMULIN 70/30 is present in human milk. Insulin orally ingested is degraded in the gastrointestinal tract. No adverse reactions associated with infant exposure to insulin through the consumption of human milk have been reported. Good glucose control supports lactation in patients with diabetes. Women with diabetes who are lactating may require adjustments in their insulin dose.

8.4 Pediatric Use

Safety and effectiveness of HUMULIN 70/30 in patients less than 18 years of age has not been established.

8.5 Geriatric Use

The effect of age on the pharmacokinetics and pharmacodynamics of HUMULIN 70/30 has not been studied [see Clinical Pharmacology (12.3)]. Patients with advanced age using any insulin, including HUMULIN 70/30, may be at increased risk of hypoglycemia due to co-morbid disease and polypharmacy [see Warnings and Precautions (5.3)].

8.6 Renal Impairment

The effect of renal impairment on the pharmacokinetics and pharmacodynamics of HUMULIN 70/30 has not been studied [see Clinical Pharmacology (12.3)]. Patients with renal impairment are at increased risk of hypoglycemia and may require more frequent HUMULIN 70/30 dose adjustment and more frequent blood glucose monitoring.

8.7 Hepatic Impairment

The effect of hepatic impairment on the pharmacokinetics and pharmacodynamics of HUMULIN 70/30 has not been studied [see Clinical Pharmacology (12.3)]. Patients with hepatic impairment are at increased risk of hypoglycemia and may require more frequent HUMULIN 70/30 dose adjustment and more frequent blood glucose monitoring.

10 OVERDOSAGE

Excess insulin administration may cause hypoglycemia and hypokalemia [see Warnings and Precautions (5.3, 5.5)]. Mild episodes of hypoglycemia can be treated with oral glucose. Adjustments in drug dosage, meal patterns, or physical activity level may be needed. More severe episodes with coma, seizure, or neurologic impairment may be treated with intramuscular/subcutaneous glucagon or concentrated intravenous glucose. Sustained carbohydrate intake and observation may be necessary because hypoglycemia may recur after apparent clinical recovery. Hypokalemia must be corrected appropriately.

11 DESCRIPTION

HUMULIN 70/30 (70% human insulin isophane suspension and 30% human insulin injection [rDNA origin]) is a human insulin suspension. Human insulin is produced by recombinant DNA technology utilizing a non-pathogenic laboratory strain of Escherichia coli. HUMULIN 70/30 is a suspension of crystals produced from combining human insulin and protamine sulfate under appropriate conditions for crystal formation and mixing with human insulin injection. The amino acid sequence of HUMULIN 70/30 is identical to human insulin and has the empirical formula C257H383N65O77S6 with a molecular weight of 5808.

HUMULIN 70/30 is a sterile white suspension. Each milliliter of HUMULIN 70/30 contains 100 units of insulin human, 0.24 mg of protamine sulfate, 16 mg of glycerin, 3.78 mg of dibasic sodium phosphate, 1.6 mg of metacresol, 0.65 mg of phenol, zinc oxide content adjusted to provide 0.025 mg zinc ion, and Water for Injection. The pH is 7.0 to 7.8. Sodium hydroxide and/or hydrochloric acid may be added during manufacture to adjust the pH.

12 CLINICAL PHARMACOLOGY

12.1 Mechanism of Action

HUMULIN 70/30 lowers blood glucose by stimulating peripheral glucose uptake by skeletal muscle and fat, and by inhibiting hepatic glucose production. Insulins inhibit lipolysis and proteolysis, and enhance protein synthesis.

12.2 Pharmacodynamics

HUMULIN 70/30 combines an intermediate-acting insulin with the more rapid onset of action of regular human insulin. In healthy males (n=18) given HUMULIN 70/30 (0.3 unit/kg) subcutaneously, the pharmacologic effect began at approximately 50 minutes (range: 30 to 90 minutes) (see Figure 1). The effect was maximal at approximately 3.5 hours (range: 1.5 to 6.5 hours) and the mean duration of action was relatively long (approximately 23 hours; range: 18-24 hours).

Figure 1 should be considered only as a representative example since the time course of action of insulin may vary in different individuals or within the same individual. The rate of insulin absorption and consequently the onset of activity is known to be affected by the site of injection, physical activity level, and other variables [see Warnings and Precautions (5.3)].

Figure 1: Mean Insulin Activity Versus Time Profiles After Subcutaneous Injection of HUMULIN 70/30 or HUMULIN® R U‑100 (0.3 unit/kg) in Healthy Subjects.

12.3 Pharmacokinetics

Absorption — In healthy male subjects given HUMULIN 70/30 (0.3 unit/kg) subcutaneously, the mean peak serum concentration occurred at 2.2 hours (range: 1 to 5 hours) after dosing.

Metabolism — The uptake and degradation of insulin occurs predominantly in liver, kidney, muscle, and adipocytes, with the liver being the major organ involved in the clearance of insulin.

Elimination — Because of the absorption-rate limited kinetics of insulin mixtures, a true half-life cannot be accurately estimated from the terminal slope of the concentration versus time curve.

Specific Populations

The effects of age, gender, race, obesity, pregnancy, or smoking on the pharmacokinetics of HUMULIN 70/30 have not been studied.

Careful glucose monitoring and dose adjustments of insulin, including HUMULIN 70/30, may be necessary in patients with renal or hepatic dysfunction [see Use in Specific Populations (8.6, 8.7)].

13 NONCLINICAL TOXICOLOGY

13.1 Carcinogenesis, Mutagenesis, Impairment of Fertility

Carcinogenicity and fertility studies were not performed in animals. Biosynthetic human insulin was not genotoxic in the in vivo sister chromatid exchange assay and the in vitro gradient plate and unscheduled DNA synthesis assays.

16 HOW SUPPLIED/STORAGE AND HANDLING

Product: 50090-0444

NDC: 50090-0444-0 10 mL in a VIAL

17 PATIENT COUNSELING INFORMATION

Advise the patient to read the FDA-approved patient labeling (Patient Information and Instructions for Use).

Never Share a HUMULIN 70/30 KwikPen or Syringe Between Patients

Advise patients that they must never share a HUMULIN 70/30 KwikPen with another person, even if the needle is changed. Advise patients using HUMULIN 70/30 vials not to share needles or syringes with another person. Sharing poses a risk for transmission of blood-borne pathogens.

Hypoglycemia

Instruct patients on self-management procedures including glucose monitoring, proper injection technique, and management of hypoglycemia and hyperglycemia especially at initiation of HUMULIN 70/30 therapy. Instruct patients on handling of special situations such as intercurrent conditions (illness, stress, or emotional disturbances), an inadequate or skipped insulin dose, inadvertent administration of an increased insulin dose, inadequate food intake, and skipped meals. Instruct patients on the management of hypoglycemia.

Inform patients that their ability to concentrate and react may be impaired as a result of hypoglycemia. Advise patients who have frequent hypoglycemia or reduced or absent warning signs of hypoglycemia to use caution when driving or operating machinery [see Warnings and Precautions (5.3)].

Inform patients that accidental mix-ups between HUMULIN 70/30 and other insulins have been reported. Instruct patients to always carefully check that they are administering the correct insulin (e.g., by checking the insulin label before each injection) to avoid medication errors between HUMULIN 70/30 and other insulins.

Hypersensitivity Reactions

Advise patients that hypersensitivity reactions have occurred with HUMULIN 70/30. Inform patients on the symptoms of hypersensitivity reactions [see Warnings and Precautions (5.4)].

Females with Reproductive Potential

Advise females of reproductive potential with diabetes to inform their doctor if they are pregnant or are contemplating pregnancy [see Use in Specific Populations (8.1)].

Visual Inspection Prior to Use

Instruct patients to visually inspect HUMULIN 70/30 before use and to use HUMULIN 70/30 only if it contains no particulate matter and appears uniformly cloudy after mixing [see Dosage and Administration (2.1)].

Expiration Date

Instruct patients not to use HUMULIN 70/30 after the printed expiration date.

____________

HUMULIN® and HUMULIN® 70/30 KwikPen® are trademarks of Eli Lilly and Company.

Literature revised July 11, 2017

Marketed by: Lilly USA, LLC, Indianapolis, IN 46285, USA
Copyright © 1992, 2017, Eli Lilly and Company. All rights reserved.

LIN7030-0002-USPI-20170711

PATIENT INFORMATION
HUMULIN® (HU-mu-lin) 70/30
(70% human insulin isophane suspension and
30% human insulin injection [rDNA origin])

Do not share your HUMULIN 70/30 KwikPen or syringes with other people, even if the needle has been changed. You may give other people a serious infection or get a serious infection from them.

What is HUMULIN 70/30?

- HUMULIN 70/30 is a man-made insulin that is used to control high blood sugar in adults with diabetes mellitus.

Who should not use HUMULIN 70/30?

Do not use HUMULIN 70/30 if you:

- are having an episode of low blood sugar (hypoglycemia).
- have an allergy to HUMULIN 70/30 or any of the ingredients in HUMULIN 70/30.

Before using HUMULIN 70/30, tell your healthcare provider about all your medical conditions including, if you:

- have liver or kidney problems.
- take any other medicines, especially ones commonly called TZDs (thiazolidinediones).
- have heart failure or other heart problems. If you have heart failure, it may get worse while you take TZDs with HUMULIN 70/30.
- are pregnant, planning to become pregnant, or are breastfeeding.
- are taking new prescription or over-the-counter medicines, vitamins, or herbal supplements.

Before you start using HUMULIN 70/30, talk to your healthcare provider about low blood sugar and how to manage it.

How should I use HUMULIN 70/30?

- Read the Instructions for Use that come with your HUMULIN 70/30.
- Use HUMULIN 70/30 exactly as your healthcare provider tells you to.
- Know the type and strength of insulin you use. Do not change the type of insulin you use unless your healthcare provider tells you to. The amount of insulin and the best time for you to take your insulin may need to change if you use different types of insulin.
- Check your blood sugar levels. Ask your healthcare provider what your blood sugars should be and when you should check your blood sugar levels.
- Do not share your HUMULIN 70/30 KwikPen or syringes with other people, even if the needle has been changed. You may give other people a serious infection or get a serious infection from them.

Your HUMULIN 70/30 dose may need to change because of:

- change in level of physical activity or exercise, weight gain or loss, increased stress, illness, change in diet.

What should I avoid while using HUMULIN 70/30?

While using HUMULIN 70/30 do not:

- Drive or operate heavy machinery, until you know how HUMULIN 70/30 affects you.
- Drink alcohol or use prescription or over-the-counter medicines that contain alcohol.

What are the possible side effects of HUMULIN 70/30?

HUMULIN 70/30 may cause serious side effects that can lead to death, including:

- low blood sugar (hypoglycemia). Signs and symptoms that may indicate low blood sugar include:
  - dizziness or light-headedness, sweating, confusion, headache, blurred vision, slurred speech, shakiness, fast heartbeat, anxiety, irritability, or mood changes, hunger.
- serious allergic reaction (whole body reaction). Get medical help right away, if you have any of these symptoms of an allergic reaction:
  - a rash over your whole body, trouble breathing, a fast heartbeat, or sweating.
- low potassium in your blood (hypokalemia).
- heart failure. Taking certain diabetes pills called thiazolidinediones or “TZDs” with HUMULIN 70/30 may cause heart failure in some people. This can happen even if you have never had heart failure or heart problems before. If you already have heart failure it may get worse while you take TZDs with HUMULIN 70/30. Your healthcare provider should monitor you closely while you are taking TZDs with HUMULIN 70/30. Tell your healthcare provider if you have any new or worse symptoms of heart failure including:
  - shortness of breath, swelling of your ankles or feet, sudden weight gain
    Treatment with TZDs and HUMULIN 70/30 may need to be adjusted or stopped by your healthcare provider if you have new or worse heart failure.

Get emergency medical help if you have:

- trouble breathing, shortness of breath, fast heartbeat, swelling of your face, tongue, or throat, sweating, extreme drowsiness, dizziness, confusion.

The most common side effects of HUMULIN 70/30 include:

- low blood sugar (hypoglycemia), allergic reactions including reactions at the injection site, skin thickening or pits at the injection site (lipodystrophy), itching, rash, weight gain, and swelling of your hands and feet. These are not all the possible side effects of HUMULIN 70/30. Call your doctor for medical advice about side effects. You may report side effects to FDA at 1-800-FDA-1088.

General information about the safe and effective use of HUMULIN 70/30:

Medicines are sometimes prescribed for purposes other than those listed in a Patient Information leaflet. You can ask your pharmacist or healthcare provider for information about HUMULIN 70/30 that is written for health professionals. Do not use HUMULIN 70/30 for a condition for which it was not prescribed. Do not give HUMULIN 70/30 to other people, even if they have the same symptoms that you have. It may harm them.

What are the ingredients in HUMULIN 70/30?

Active Ingredient: insulin human (rDNA origin)

Inactive Ingredients: protamine sulfate, glycerin, dibasic sodium phosphate, metacresol, phenol, zinc oxide, water for injection, hydrochloric acid or sodium hydroxide

For more information, call 1-800-545-5979 or go to www.humulin.com.

This Patient Information has been approved by the U.S. Food and Drug Administration.

Patient Information revised July 11, 2017

Marketed by: Lilly USA, LLC, Indianapolis, IN 46285, USA
Copyright © 1992, 2017, Eli Lilly and Company. All rights reserved.

LIN7030-0002-PPI-20170711

Instructions for Use
HUMULIN® (HU-mu-lin) 70/30
(70% human insulin isophane suspension and
30% human insulin injection [rDNA origin])
vial (100 Units/mL, U-100)

Read the Instructions for Use before you start taking HUMULIN 70/30 and each time you get a new HUMULIN 70/30 vial. There may be new information. This information does not take the place of talking to your healthcare provider about your medical condition or your treatment.

Do not share your syringes with other people, even if the needle has been changed. You may give other people a serious infection or get a serious infection from them.

Supplies needed to give your injection:

- a HUMULIN 70/30 vial
- a U-100 insulin syringe and needle
- 2 alcohol swabs
- 1 sharps container for throwing away used needles and syringes. See “Disposing of used needles and syringes” at the end of these instructions.

Preparing your HUMULIN 70/30 dose:

- Wash your hands with soap and water.
- Check the HUMULIN 70/30 label to make sure you are taking the right type of insulin. This is especially important if you use more than 1 type of insulin.
- Do not use HUMULIN 70/30 past the expiration date printed on the label or 31 days after you first use it.
- Always use a new syringe or needle for each injection to help ensure sterility and prevent blocked needles. Do not reuse or share your syringes or needles with other people. You may give other people a serious infection or get a serious infection from them.

Step 1:
Gently roll the vial between the palms of your hands at least 10 times.

Step 2:
Carefully invert the vial at least 10 times.
Mixing is important to make sure you get the right dose. Humulin 70/30 should look white and cloudy after mixing. Do not use it if it looks clear or contains any lumps or particles.

Step 3:
If you are using a new vial, pull off the plastic Protective Cap, but do not remove the Rubber Stopper.

Step 4:
Wipe the Rubber Stopper with an alcohol swab.

Step 5:
Hold the syringe with the needle pointing up. Pull down on the Plunger until the tip of the Plunger reaches the line for the number of units for your prescribed dose.

(Example Dose: 20 units shown)

Step 6:
Push the needle through the Rubber Stopper of the vial.

Step 7:
Push the plunger all the way in. This puts air into the vial.

Step 8:
Turn the vial and syringe upside down and slowly pull the Plunger down until the tip is a few units past the line for your prescribed dose.
If there are air bubbles, tap the syringe gently a few times to let any air bubbles rise to the top.

(Example Dose: 20 units Plunger is shown at 24 units)

Step 9:
Slowly push the Plunger up until the tip reaches the line for your prescribed dose.
Check the syringe to make sure that you have the right dose.

(Example Dose: 20 units shown)

Step 10:
Pull the syringe out of the vial's Rubber Stopper.

Giving your HUMULIN 70/30 injection:

- Inject your insulin exactly as your healthcare provider has shown you.
- Change (rotate) your injection site for each injection.

Step 11:
Choose your injection site.
HUMULIN 70/30 is injected under the skin (subcutaneously) of your stomach area (abdomen), buttocks, upper legs or upper arms.
Wipe the skin with an alcohol swab. Let the injection site dry before you inject your dose.

Step 12:
Insert the needle into your skin.

Step 13:
Push down on the Plunger to inject your dose.
The needle should stay in your skin for at least 5 seconds to make sure you have injected all of your insulin dose.

Step 14:
Pull the needle out of your skin.

- If you see blood after you take the needle out of your skin, press the injection site with a piece of gauze or an alcohol swab. Do not rub the area.
- Do not recap the needle. Recapping the needle can lead to a needle stick injury.

Disposing of used needles and syringes:

- Put your used needles and syringes in a FDA-cleared sharps disposal container right away after use. Do not throw away (dispose of) loose needles and syringes in your household trash.
- If you do not have a FDA-cleared sharps disposal container, you may use a household container that is:
  - made of a heavy-duty plastic,
  - can be closed with a tight-fitting, puncture-resistant lid, without sharps being able to come out,
  - upright and stable during use,
  - leak-resistant, and
  - properly labeled to warn of hazardous waste inside the container.
- When your sharps disposal container is almost full, you will need to follow your community guidelines for the right way to dispose of your sharps disposal container. There may be state or local laws about how you should throw away used needles and syringes. For more information about safe sharps disposal, and for specific information about sharps disposal in the state that you live in, go to the FDA's website at: http://www.fda.gov/safesharpsdisposal.
- Do not dispose of your used sharps disposal container in your household trash unless your community guidelines permit this. Do not recycle your used sharps disposal container.

How should I store HUMULIN 70/30?

All unopened HUMULIN 70/30 vials:

- Store all unopened vials in the refrigerator.
- Do not freeze. Do not use if it has been frozen.
- Keep away from heat and out of direct light.
- Unopened vials can be used until the expiration date on the carton and label, if they have been stored in the refrigerator.
- Unopened vials should be thrown away after 31 days, if they are stored at room temperature.

After HUMULIN 70/30 vials have been opened:

- Store opened vials in the refrigerator or at room temperature below 86°F (30°C) for up to 31 days.
- Keep away from heat and out of direct light.
- Throw away all opened vials after 31 days of use, even if there is still insulin left in the vial.

General information about the safe and effective use of HUMULIN 70/30.

- Keep HUMULIN 70/30 vials, syringes, needles, and all medicines out of the reach of children.
- Always use a new syringe or needle for each injection.
- Do not reuse or share your syringes or needles with other people. You may give other people a serious infection or get a serious infection from them.

If you have any questions or problems with your HUMULIN, contact Lilly at 1-800-Lilly-Rx (1-800-545-5979) or call your healthcare provider for help. For more information on HUMULIN and insulin, go to www.humulin.com.

Scan this code to launch the humulin.com website

This Instructions for Use has been approved by the U.S. Food and Drug Administration.

Humulin® is a trademark of Eli Lilly and Company.

Instructions for Use revised: September 24, 2015

Marketed by: Lilly USA, LLC, Indianapolis, IN 46285, USA
Copyright © 1992, 2015, Eli Lilly and Company. All rights reserved.

LIN7030VL-0002-IFU-20150924

Instructions for Use

HUMULIN® 70/30 KwikPen®

(70% human insulin isophane suspension
30% human insulin injection [rDNA origin])

100 units/mL, 3 mL pen

Read the Instructions for Use before you start taking HUMULIN 70/30 and each time you get another KwikPen. There may be new information. This information does not take the place of talking to your healthcare provider about your medical condition or your treatment.

Do not share your HUMULIN 70/30 KwikPen with other people, even if the needle has been changed. You may give other people a serious infection or get a serious infection from them.

HUMULIN® 70/30 KwikPen® (“Pen”) is a disposable prefilled pen containing 300 units of HUMULIN 70/30. You can give yourself more than 1 dose from the Pen. Each turn (click) of the Dose Knob dials 1 unit of insulin. You can give from 1 to 60 units in a single injection. If your dose is more than 60 units, you will need to give yourself more than 1 injection. The Plunger only moves a little with each injection, and you may not notice that it moves. The Plunger will only reach the end of the cartridge when you have used all 300 units in the Pen.

This Pen is not recommended for use by the blind or visually impaired without the help of someone trained to use the Pen.

How to recognize your HUMULIN 70/30 KwikPen

- Pen color: Beige
- Dose Knob: Brown
- Labels: White label with brown stripe

Supplies you will need to give your injection

- HUMULIN 70/30 KwikPen
- KwikPen compatible Needle (Becton, Dickinson and Company Pen Needles recommended)
- Alcohol swab
- Gauze

Preparing your Pen

- Wash your hands with soap and water.
- Check your Pen to make sure you are taking the right type of insulin. This is especially important if you use more than 1 type of insulin.
- Do not use your Pen past the expiration date printed on the Label or for more than 10 days after you first start using the Pen.
- Always use a new needle for each injection to help prevent infections and blocked needles. Do not reuse or share your needles with other people. You may give other people a serious infection or get a serious infection from them.

Step 1:

- Pull the Pen Cap straight off.
  - Do not remove the Pen Label.
- Wipe the Rubber Seal with an alcohol swab.
  - Do not attach the Needle before mixing.

Step 2:

- Gently roll the Pen between your hands 10 times.

Step 3:

- Move the Pen up and down (invert) 10 times.
  Mixing by rolling and inverting the Pen is important to make sure you get the right dose.

Step 4:

- Check the liquid in the Pen. HUMULIN 70/30 should look white and cloudy after mixing. Do not use if it looks clear or has any lumps or particles in it.

Step 5:

- Select a new Needle.
- Pull off the Paper Tab from the Outer Needle Shield.

Step 6:

- Push the capped Needle straight onto the Pen and twist the Needle on until it is tight.

Step 7:

- Pull off the Outer Needle Shield. Do not throw it away.
- Pull off the Inner Needle Shield and throw it away.

Priming your Pen

Prime before each injection.

- Priming your Pen means removing the air from the Needle and Cartridge that may collect during normal use and ensures that the Pen is working correctly.
- If you do not prime before each injection, you may get too much or too little insulin.

Step 8:

- To prime your Pen, turn the Dose Knob to select 2 units.

Step 9:

- Hold your Pen with the Needle pointing up. Tap the Cartridge Holder gently to collect air bubbles at the top.

Step 10:

- Continue holding your Pen with Needle pointing up. Push the Dose Knob in until it stops, and “0” is seen in the Dose Window. Hold the Dose Knob in and count to 5 slowly.
- You should see insulin at the tip of the Needle.
  - If you do not see insulin, repeat priming steps 8 to 10, no more than 4 times.
  - If you still do not see insulin, change the Needle and repeat priming steps 8 to 10.

Small air bubbles are normal and will not affect your dose.

Selecting your dose

- You can give from 1 to 60 units in a single injection.
- If your dose is more than 60 units, you will need to give more than 1 injection.
  - If you need help with dividing up your dose the right way, ask your healthcare provider.
  - Use a new Needle for each injection and repeat the priming step.

Step 11:

- Turn the Dose Knob to select the number of units you need to inject. The Dose Indicator should line up with your dose.
  - The Pen dials 1 unit at a time.
  - The Dose Knob clicks as you turn it.
  - Do not dial your dose by counting the clicks. You may dial the wrong dose. This may lead to you getting too much insulin or not enough insulin.
  - The dose can be corrected by turning the Dose Knob in either direction until the correct dose lines up with the Dose Indicator.
  - The even numbers (for example, 12) are printed on the dial.
  - The odd numbers, (for example, 25) after the number 1, are shown as full lines.
- Always check the number in the Dose Window to make sure you have dialed the correct dose.

(Example: 12 units shown in the Dose Window)
(Example: 25 units shown in the Dose Window)

- The Pen will not let you dial more than the number of units left in the Pen.
- If you need to inject more than the number of units left in the Pen, you may either:
  - inject the amount left in your Pen and then use a new Pen to give the rest of your dose,
  or
  - get a new Pen and inject the full dose.
- It is normal to see a small amount of insulin left in the Pen that you can not inject.

Giving your injection

- Inject your insulin as your healthcare provider has shown you.
- Change (rotate) your injection site for each injection.
- Do not try to change your dose while injecting.

Step 12:

- Choose your injection site.
  HUMULIN 70/30 is injected under the skin (subcutaneously) of your stomach area, buttocks, upper legs or upper arms.
- Wipe your skin with an alcohol swab, and let your skin dry before you inject your dose.

Step 13:

- Insert the Needle into your skin.
- Push the Dose Knob all the way in.
- Continue to hold the Dose Knob in and slowly count to 5 before removing the Needle.

Do not try to inject your insulin by turning the Dose Knob. You will not receive your insulin by turning the Dose Knob.

Step 14:

- Pull the Needle out of your skin.
  A drop of insulin at the Needle tip is normal. It will not affect your dose.
- Check the number in the Dose Window.
  - If you see “0” in the Dose Window, you have received the full amount you dialed.
  - If you do not see “0” in the Dose Window, do not redial. Insert the Needle into your skin and finish your injection.
  - If you still do not think you received the full amount you dialed for your injection, do not start over or repeat the injection. Monitor your blood glucose as instructed by your healthcare provider.
  - If you normally need to give 2 injections for your full dose, be sure to give your second injection.

The Plunger only moves a little with each injection, and you may not notice that it moves.
If you see blood after you take the Needle out of your skin, press the injection site lightly with a piece of gauze or an alcohol swab. Do not rub the area.

After your injection

Step 15:

- Carefully replace the Outer Needle Shield.

Step 16:

- Unscrew the capped Needle and throw it away (see Disposing of Pens and Needles section).
- Do not store the Pen with the Needle attached to prevent leaking, blocking the Needle, and air from entering the Pen.

Step 17:

- Replace the Pen Cap by lining up the Cap Clip with the Dose Indicator and pushing straight on.

Disposing of Pens and Needles

- Put your used needles in a FDA-cleared sharps disposal container right away after use. Do not throw away (dispose of) loose needles in your household trash.
- If you do not have a FDA-cleared sharps disposal container, you may use a household container that is:
  - made of a heavy-duty plastic,
  - can be closed with a tight-fitting, puncture-resistant lid, without sharps being able to come out,
  - upright and stable during use,
  - leak-resistant, and
  - properly labeled to warn of hazardous waste inside the container.
- When your sharps disposal container is almost full, you will need to follow your community guidelines for the right way to dispose of your sharps disposal container. There may be state or local laws about how you should throw away used needles and syringes. For more information about safe sharps disposal, and for specific information about sharps disposal in the state that you live in, go to the FDA's website at: http://www.fda.gov/safesharpsdisposal
- Do not dispose of your used sharps disposal container in your household trash unless your community guidelines permit this. Do not recycle your used sharps disposal container.
- The used Pen may be discarded in your household trash after you have removed the needle.

Storing your Pen

Unused Pens

- Store unused Pens in the refrigerator at 36°F to 46°F (2°C to 8°C).
- Do not freeze your insulin. Do not use if it has been frozen.
- Unused Pens may be used until the expiration date printed on the Label, if the Pen has been kept in the refrigerator.

In-use Pen

- Store the Pen you are currently using at room temperature [up to 86°F (30°C)]. Keep away from heat and light.
- Throw away the HUMULIN 70/30 Pen you are using after 10 days, even if it still has insulin left in it.

General information about the safe and effective use of your Pen

- Keep your Pen and needles out of the reach of children.
- Do not use your Pen if any part looks broken or damaged.
- Always carry an extra Pen in case yours is lost or damaged.

Troubleshooting

- If you can not remove the Pen Cap, gently twist the cap back and forth, and then pull the cap straight off.
- If the Dose Knob is hard to push:
  - Pushing the Dose Knob more slowly will make it easier to inject.
  - Your Needle may be blocked. Put on a new Needle and prime the Pen.
  - You may have dust, food, or liquid inside the Pen. Throw the Pen away and get a new Pen.

If you have any questions or problems with your HUMULIN 70/30 KwikPen, contact Lilly at 1-800-LillyRx (1-800-545-5979) or call your healthcare provider for help. For more information on HUMULIN 70/30 KwikPen and insulin, go to www.lilly.com.

Scan this code to launch

www.humulin.com

This Instructions for Use has been approved by the U.S. Food and Drug Administration.

HUMULIN® and HUMULIN® KwikPen® are trademarks of Eli Lilly and Company.

Revised: January 6, 2017

Marketed by: Lilly USA, LLC
Indianapolis, IN 46285, USA

Copyright © 2013, 2017, Eli Lilly and Company. All rights reserved.

HUMULIN 70/30 KwikPen meets the current dose accuracy and functional requirements of ISO 11608-1:2014.

LIN7030KP-0003-IFU-20170106

INACTIVE INGREDIENT

protamine sulfate, glycerin, dibasic sodium phosphate, metacresol, phenol, zinc oxide, water for injection, hydrochloric acid or sodium hydroxide

ACTIVE INGREDIENT

insulin human (rDNA origin)